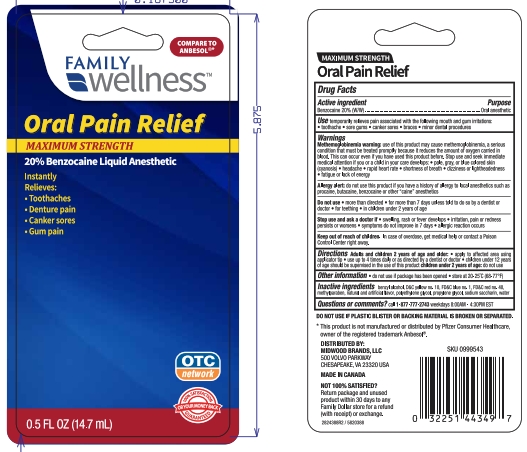 DRUG LABEL: Family Dollar
NDC: 55319-388 | Form: LIQUID
Manufacturer: Family Dollar Services Inc.
Category: otc | Type: HUMAN OTC DRUG LABEL
Date: 20230613

ACTIVE INGREDIENTS: BENZOCAINE 20 g/100 g
INACTIVE INGREDIENTS: PROPYLENE GLYCOL; POLYETHYLENE GLYCOL, UNSPECIFIED; BENZYL ALCOHOL; SACCHARIN SODIUM; FD&C RED NO. 40; D&C YELLOW NO. 10; WATER; METHYLPARABEN; FD&C BLUE NO. 1

5820388 Family Wellness Max Str Oral Pain Relief

Drug Facts

Active ingredient

Benzocaine 20% (W/W)

Purpose

Oral anesthetic

Use

Temporarily relieves pain associated with the following mouth and gum irritations:

- toothache
- sore gums
- canker sores
- braces
- minor dental procedures

Warnings

Methemoglobinemia warning: use of this product may cause methemoglobinemia, a serious condition that must be treated promptly because it reduces the amount of oxygen carried in blood. This can occur even if you have used this product before. Stop use and seek immediate medical attention if you or a child in your care develops:

- pale, gray, or blue colored skin(cyanosis)
- headache
- rapid heart rate
- shortness of breath
- dizziness or lightheadedness
- fatigue or lack of energy

Allergy alert: do not use this product if you have a history of allergy to local anesthetics such as procaine, butacaine, benzocaine or other “caine” anesthetics

Do not use

- more than directed
- for more than 7 days unless told to do so by a dentist or doctor
- for teething
- in children under 2 years of age

Stop use and ask a doctor if

- swelling, rash or fever develops
- irritation, pain or redness persists or worsens
- symptoms do not improve in 7 days
- allergic reaction occurs

Keep out of reach of children. In case of overdose, get medical help or contact a Poison Control Center right away.

Directions

Adults and children 2 years of age and older:

- apply to affected area using applicator tip
- use up to 4 times daily or as directed by a dentist or doctor
- children under 12 years of age should be supervised in the use of this product

children under 2 years of age: do not use

Other information

- do not use if package has been opened
- store at 20 - 25 C (68-77F)

INACTIVE INGREDIENT

Inactive ingredients Benzyl Alcohol, D&C Yellow no. 10, FD&C Blue no. 1, FD&C Red no. 40, Methylparaben, Natural and Artificial Flavor, Polyethylene Glycol, Propylene Glycol, Sodium Saccharin, Water

MADE IN CANADA

DISTRIBUTED BY:

MIDWOOD BRANDS, LLC

10611 MONROE RD.

MATTHEWS, NC 28105

PACKAGE LABEL

FAMILY WELLNESS

MAXIMUM STRENGTH

Oral Pain Relief

20% Benzocaine

Liquid Anesthetic

0.5 FL OZ (14.7 mL)